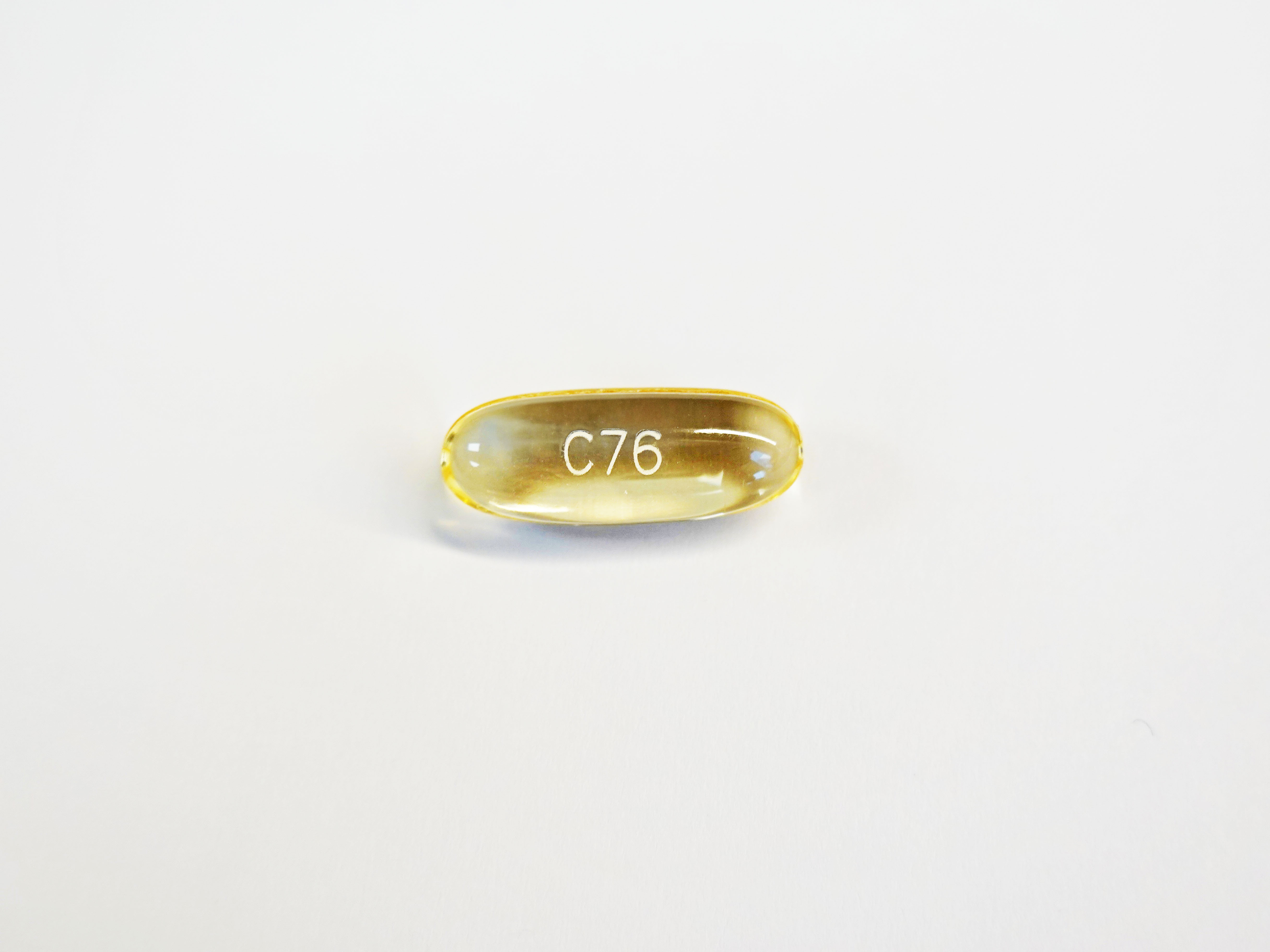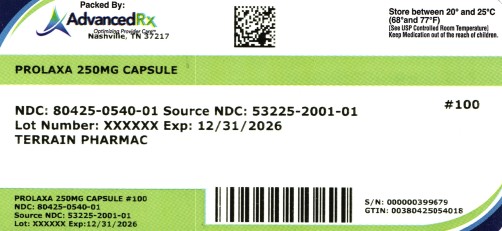 DRUG LABEL: Prolaxa
NDC: 80425-0540 | Form: CAPSULE, LIQUID FILLED
Manufacturer: Advanced Rx of Tennessee, LLC
Category: otc | Type: HUMAN OTC DRUG LABEL
Date: 20250805

ACTIVE INGREDIENTS: DOCUSATE SODIUM 250 mg/1 1
INACTIVE INGREDIENTS: GELATIN; SORBITAN; PROPYLENE GLYCOL; GLYCERIN; POLYETHYLENE GLYCOL, UNSPECIFIED

Prolaxa

Active ingredient (in each softgel)

Docusate sodium 250 mg - Extra Strength

Purpose

Stool softener laxative

Uses

- for relief of occasional constipation
- this product generally produces a bowel movement within 12 to 72 hours

Warnings

Do not use

if you are presently taking mineral oil, unless directed by a doctor.

Ask a doctor before use if you have

- stomach pain
- nausea
- vomiting
- noticed a sudden change in bowel habits that last over 2 weeks

Stop use and ask a doctor if

- you have rectal bleeding or fail to have a bowel movement after use of a laxative. These could be signs of a serious condition.
- you need to use a laxative for more than 1 week

If pregnant or breast-feeding

ask a health professional before use.

Keep out of reach of children.

In case of overdose, get medical help or contact a Poison Control Center right away.

Directions

- adults and children 12 years of age and over: take 1 softgel daily or as directed by a doctor
- children under 12 years of age: ask a doctor

Other information

- store between 20-25ºC(68-77ºF); excursions permitted between 15-30ºC (59-86ºF)

Inactive Ingredients

GELATIN, GLYCERIN, POLYETHYLENE GLYCOL, PROPYLENE GLYCOL, SORBITAN

Questions or comments?

Call toll free (877) 985-8377 or info@terrainrx.com

Prolaxa™

Stool Softener

DOCUSATE SODIUM, 250 mg

STOOL SOFTENER LAXATIVE - SOFTGELS

- MAXIMUM STRENGTH
- Easy to swallow
- Relieves constipation
- Gentle Relieve
- Dependable
- Stimulant Free

TAMPER EVIDENT: DO NOT USE IF PRINTED SAFETY SEAL UNDER CAP IS BROKEN OR MISSING.